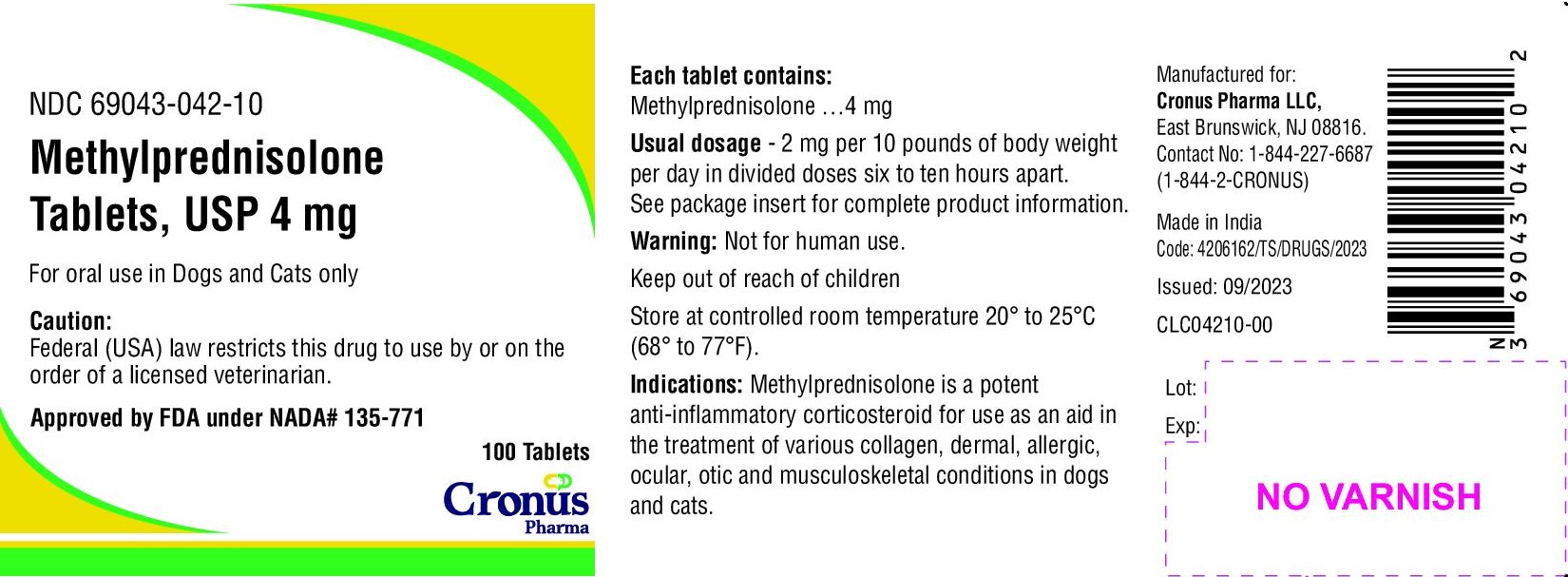 DRUG LABEL: methylprednisolone
NDC: 69043-042 | Form: TABLET
Manufacturer: Cronus Pharma LLC
Category: animal | Type: PRESCRIPTION ANIMAL DRUG LABEL
Date: 20240103

ACTIVE INGREDIENTS: METHYLPREDNISOLONE 4 mg/1 1

Methylprednisolone Tablets, USP
For Oral Use in Dogs and Cats Only
CAUTION: Federal law restricts this drug to use by or on the order of a licensed veterinarian.

DESCRIPTION

Methylprednisolone, a potent glucocorticoid and anti-inflammatory agent, is a synthetic 6-methyl derivative of prednisolone. It has a greater anti-inflammatory potency than prednisolone and is less likely to induce sodium and water retention. Its advantage over the older corticoids lies in its ability to achieve equal anti-inflammatory effect with a lower dose, while at the same time enhancing the split between anti-inflammatory and mineralocorticoid activities. ^1,2,3

Each tablet contains 1mg, 2mg or 4mg of methylprednisolone.

ACTIONS

Glucocorticoids exert a regulatory influence on lymphocytes, erythrocytes and eosinophils of the blood and on the structure and function of lymphoid tissues.^1,4,5 A primary feature of the glucocorticoids is their anti-inflammatory activity with minimum sodium and water retention which is often associated with the mineralocorticoids. ^1,2,3,4,5,6 Glucocorticoids not only inhibit the early phases of the inflammatory process (edema, fibrin deposition, capillary dilation, migration of leukocytes into the inflamed area and phagocytic activity) but also the later manifestations (capillary proliferation, fibroblast proliferation and deposition of collagen). ^3,4,6 The exact mechanism is not known, but the glucocorticoids obviously suppress normal tissue response to injury and alleviate symptoms from many conditions. ^2

INDICATIONS

The indications are the same as those for other anti-inflammatory steroids and comprise the various collagen, dermal, allergic, ocular, otic and musculoskeletal conditions known to be responsive to the anti-inflammatory corticosteroids. Representative of the conditions in which the use of steroid therapy and the benefits to be derived therefrom have had repeated confirmation in the veterinary literature are:

Dermal conditions, such as non-specific eczema and summer dermatics. ^1,2,4

Allergic manifestations, such as acute urticaria, allergic dermatitis, drug and serum reactions, non-specific pruritus, bronchial asthma and pollen sensitivities. ^1,2,3,4,5

Ocular Conditions, such as iritis, iridocyclitis, secondary glaucoma, uveitis and chlorioretinitis. ^1,3,4,5

Otic Conditions, such as otitis externa. ^4

Musculoskeletal Conditions, such as myositis, rheumatoid arthritis, osteoarthritis and bursitis. ^1,2,3,4,5

Various chronic or recurrent diseases of unknown etiology such as ulcerative colitis and nephrosis. ^1,2,3,5

In acute adrenal insufficiency, methylprednisolone may be effective because of its ability to correct the defect in carbohydrate metabolism and relieve the impaired diuretic response to water, characteristic of primary or secondary adrenal insufficiency. However, because this agent lacks significant mineralocorticoid activity, hydrocortisone sodium succinate or cortisone should be used when salt retention is indicated.

CONTRAINDICATIONS

Do not use in viral infections. Methylprednisolone, like prednisolone, is contraindicated in animals with arrested tuberculosis, peptic ulcer, acute psychoses, corneal ulcer and Cushingoid syndrome. The presence of diabetes, osteoporosis, chronic psychotic reactions, predisposition to thrombophlebitis, hypertension, congestive heart failure, renal insufficiency and active tuberculosis necessitates carefully controlled use. Some of the above conditions occur only rarely in dogs and cats but should be kept in mind.

WARNING

Because of its inhibitory effect on fibroplasia, methylprednisolone may mask the signs of infection and enhance dissemination of the infecting organism. Hence all animals receiving methylprednisolone should be watched for evidence of intercurrent infection. Should infection occur, it must be brought under control by use of appropriate antibacterial measures or administration of methylprednisolone should be discontinued.

Not for human use. Clinical and experimental data have demonstrated that corticosteroids administered orally or parenterally to animals may induce the first stage of parturition when administered during the last trimester of pregnancy and may precipitate premature parturition followed by dystocia, fetal death, retained placenta and metritis.

Additionally, corticosteroid administered to dogs, rabbits and rodents during pregnancy have produced cleft palate. Other congenital anomalies including deformed forelegs, phocomella and anasarca have been reported in offspring of dogs which received corticosteroids during pregnancy.

PRECAUTIONS

Methylprednisolone, like prednisolone and other adrenocortical steroids, is a potent therapeutic agent influencing the biochemical behavior of most, if not all, tissues of the body. Because this anti-inflammatory steroid manifests little sodium-retaining activity, the usual early sign of cortisone or hydrocortisone overdosage (i.e., increase in body weight due to fluid retention) is not a reliable index of overdosage. Hence, recommended dosage levels should not be exceeded, and all animals receiving methylprednisolone should be under close medical supervision. All precautions pertinent to the use of prednisolone apply to methylprednisolone. Moreover, the veterinarian should endeavor to keep informed of current studies with methylprednisolone as they are reported in the veterinary literature.

Use of corticosteroids, depending on dose, duration and specific steroid, may result in inhibition of endogenous steroid production following drug withdrawal. In patients presently receiving or recently withdrawn from systemic corticosteroid treatments, therapy with a rapid acting corticosteroid should be considered in usually stressful situations.

ADVERSE REACTIONS

Methylprednisolone is similar to prednisolone in regard to kinds of side effects and metabolic alterations to be anticipated when treatment is intensive or prolonged. In animals with diabetes mellitus, use of methylprednisolone may be associated with an increase in the insulin requirement. Negative nitrogen balance may occur, particularly in animals that require protracted maintenance therapy; measures to counteract persistent nitrogen loss include a high protein intake and the administration, when indicated, of a suitable anabolic agent. Excessive loss of potassium, like excessive retention of sodium, is not likely to be induced by effective maintenance doses of methylprednisolone. However these effects should be kept in mind and the usual regulatory measures employed as indicated. Ecchymotic manifestations, while not noted during the clinical evaluation in dogs and cats, may occur. If such reactions do occur and are serious, reduction in dosage or discontinuance of methylprednisolone therapy may be indicated. Concurrent use of daily oral supplements of ascorbic acid may be of value in helping to control ecchymotic tendencies.

Side effects, such as SAP and SGPT enzyme elevations, weight loss, anorexia, polydipsia and polyuria have occurred following the use of synthetic corticosteroids in dogs. Vomiting and diarrhea (occasionally bloody) have been observed in dogs and cats. Cushing’s syndrome in dogs has been reported in association with prolonged or repeated steroid therapy.

To report suspected adverse drug events, for technical assistance or to obtain a copy of the Safety Data Sheet, contact Cronus Pharma LLC at 1-844-227-6687 and 1-844-2-CRONUS. For additional information about adverse drug experience reporting for animal drugs, contact FDA at 1-888-FDA-VETS or http://www.fda.gov/reportanimalae.

DOSAGE AND ADMINISTRATION

The keystone of satisfactory therapeutic management with methylprednisolone, as with its steroid predecessors, is individualization of dosage in reference to the severity of the disease, the anticipated duration of steroid therapy and the animal’s threshold or tolerance for steroid excess. The prime objective of steroid therapy should be achieve a satisfactory degree of control with a minimum effective daily dose.

The dosage recommendations are suggested average total daily doses and are intended as guides. As with other orally administered corticosteroids, the total daily dose of methylprednisolone tablets should be given in equally divided doses. The initial suppressive dose level is continued until a satisfactory clinical response is obtained, a period usually of 2 to 7 days in the case of musculoskeletal diseases, allergic conditions affecting the skin or respiratory tract and ocular inflammatory diseases. If a satisfactory response is not obtained in 7 days, re-evaluation of the case to confirm the original diagnosis should be made. As soon as a satisfactory clinical response is obtained, the daily dose should be reduced gradually, either to termination of treatment in the case of acute conditions (e.g., seasonal asthma, dermatitis, acute ocular inflammations) or to the minimal effective maintenance dose level in the case of chronic conditions (e.g., rheumatoid arthritis). In chronic conditions, and in rheumatoid arthritis especially, it is important that the reduction in dosage from initial to maintenance dose levels be accomplished slowly. The maintenance dose level should be adjusted from time to time as required by fluctuation in the activity of the disease and the animal’s general status. Accumulated experience has shown that the long-term benefits to be gained from continued steroid maintenance are probably greater the lower the maintenance dose level. In rheumatoid arthritis in particular, maintenance steroid therapy should be at the lowest possible level.

IMPORTANT: In the therapeutic management of animals with chronic diseases, such as rheumatoid arthritis, methylprednisolone should be regarded as a highly valuable adjunct, to be used in conjunction with but not as a replacement for standard therapeutic measures.

RECOMMENDED DOSAGE SCHEDULE

Average total daily doses for dogs and cats are as follows:
5 to 15 lb body weight……………………………………………….2 mg
15 to 40 lb body weight………………………………………………2 to 4 mg
40 to 80 lb body weight………………………………………………4 to 8 mg
Use half tablets as needed to achieve the desired dose
The total daily dose should be given in doses, 6 to 10 hours apart.

HOW SUPPLIED

Methylprednisolone tablets, USP 1mg, 2mg are yellow round shaped scored tablets available in bottles of 100 and 500.
Methylprednisolone tablets, USP 4mg are yellow oval shaped scored tablets available in bottles of 100 and 500.

Each 1mg tablet contains 1mg methylprednisolone, USP.
Each 2mg tablet contains 2mg methylprednisolone, USP.
Each 4mg tablet contains 4mg methylprednisolone, USP.

Split tablets should be used within 90 days.
Store at controlled room temperature 20° to 25°C (68° to 77°F).

REFERENCES

1. Osol, A., ed., 1980. Remington’s Pharmaceutical Sciences, 16th Edition. Mack Publishing Company, Easton, PA. 898-901, 908.
2. Martindale, The Extra pharmacopoeia, 27th Edition, 1977. The Pharmaceutical Press, London, England. 389-396, 424-425
3. Gilman, A.G., L.S. Goodman and A. Gilman, eds., 1980. The Pharmacological Basis of Therapeutics, 6th Edition. Macmillan Publishing Co., Inc., New York. NY. 1470-1496.
4. Booth, N.H and L.E McDonald, eds., 1982. Veterinary Pharmacology and Therapeutics, 5th Edition. The lowa State University Press, Ames, IA. 553-570.
5. Dipalma, J.R., ed., 1976. Basic Pharmacology in Medicine, McGraw-Hill, Inc., St. Louis, MO 328-337.
6. Kirk, R.W., ed., 1980. Current Veterinary Therapy VII, Small Animal Practice. W.B Saunders Company. Philadelphia, PA. 497-500, 992-994.

KEEP OUT OF REACH OF CHILDREN

Approved by FDA under NADA # 135-771

Code: 4206162/TS/DRUGS/2023

Manufactured for:
Cronus Pharma LLC,
East Brunswick, NJ 08816.
Contact No: 1-844-227-6687
(1-844-2-CRONUS)

Made in India
Sepetember 2023

PACKAGE LABEL.PRINCIPAL DISPLAY PANEL

NDC 69043-040-10

Methylprednisolone Tablets, USP 4 mg

For oral use in Dogs and Cats only

Caution:

Federal (USA) law restricts this drug to use by or on the order of a licensed veterinarian.

Approved by FDA under NADA# 135-771

100 Tablets